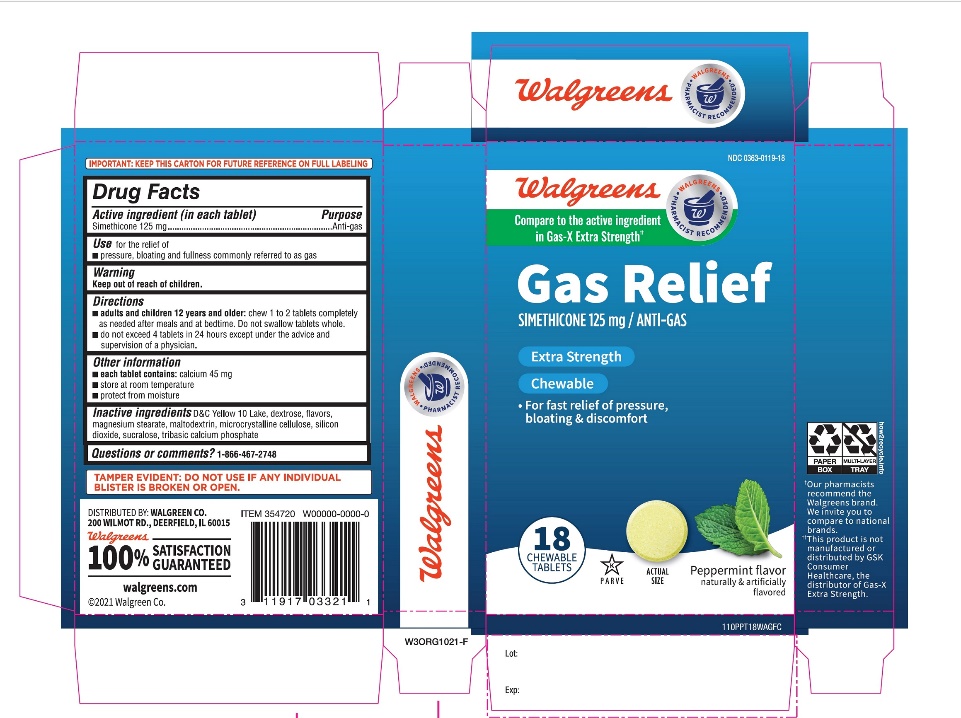 DRUG LABEL: Extra Strength Gas Relief
NDC: 0363-0119 | Form: TABLET, CHEWABLE
Manufacturer: WALGREENS CO.
Category: otc | Type: HUMAN OTC DRUG LABEL
Date: 20251125

ACTIVE INGREDIENTS: DIMETHICONE, UNSPECIFIED 125 mg/1 1
INACTIVE INGREDIENTS: D&C YELLOW NO. 10; DEXTROSE, UNSPECIFIED FORM; MAGNESIUM STEARATE; MALTODEXTRIN; MICROCRYSTALLINE CELLULOSE; SUCRALOSE; SILICON DIOXIDE; TRIBASIC CALCIUM PHOSPHATE

Extra Strength Gas Relief Tablets

Active ingredient (in each tablet)

Simethicone 125 mg

Purpose

Anti-gas

Uses

relieves pressure and bloating commonly referred to as gas

Directions

- adults:chew 1 to 2 tablets as needed after meals and at bedtime
- do not exceed 4 tablets in a 24 hour period except under the advice and supervision of a physician

Other Information

- each tablet contains :calcium 45 mg
- store at controlled room temperature 20-25°C (68-77°F)
- protect from moisture
- do not use if any individual blister unit is broken or open

Inactive Ingredients

D&C yellow # 10 lake, dextrose, flavor, magnesium stearate, maltodextrin, microcrystalline cellulose, sucralose, tribasic calcium phosphate

Principal Display Panel

WALGREENS PHARMACIST RECOMMENDED‡
NDC 0363-0119-18
EXTRA STRENGTH
Gas Relief
Simethicone 125 mg/Anti-Gas
For fast Relief of:

- Pressure
- Bloating
- Gas distress

PEPPERMINT CRÈME FLAVOR

18 Chewable Tablets

Compare to Extra Strength Gas-X® active ingredient‡‡

‡‡This product is not manufactured or distributed by Novartis Consumer Health, Inc., the distributor of Gas-X®.

IMPORTANT: Keep this carton for future reference on full labeling.